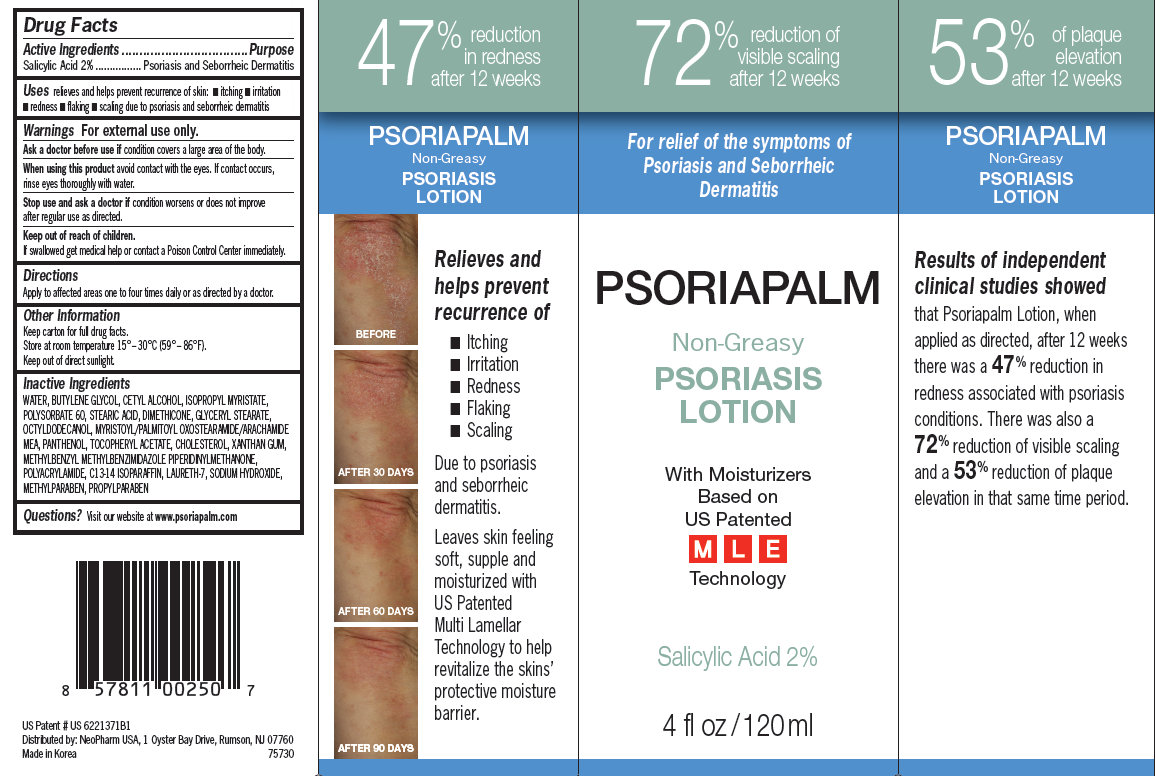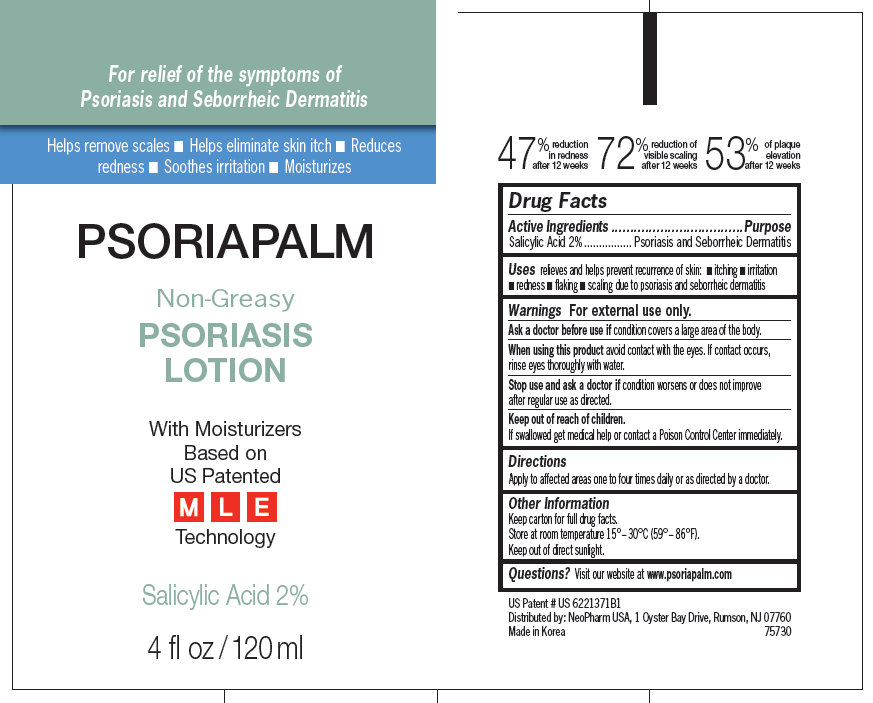 DRUG LABEL: PSORIAPALM Non-Greasy Psoriasis
NDC: 51141-8000 | Form: LOTION
Manufacturer: Neopharm Co., Ltd
Category: otc | Type: HUMAN OTC DRUG LABEL
Date: 20120704

ACTIVE INGREDIENTS: SALICYLIC ACID 2 mL/100 mL
INACTIVE INGREDIENTS: Water; Cetyl Alcohol; Butylene Glycol; Stearic Acid; Polysorbate 60; Glyceryl Monostearate; Panthenol; Methylparaben; Propylparaben; ISOPROPYL MYRISTATE; DIMETHICONE; MYRISTOYL/PALMITOYL OXOSTEARAMIDE/ARACHAMIDE MEA; .ALPHA.-TOCOPHEROL ACETATE; CHOLESTEROL; XANTHAN GUM; METHYLBENZYL METHYLBENZIMIDAZOLE PIPERIDINYLMETHANONE; C13-14 ISOPARAFFIN; LAURETH-7; SODIUM HYDROXIDE

PSORIAPALM Non-Greasy Psoriasis Lotion

PSORIAPALM Non-Greasy Psoriasis Lotion

Drug Facts

Active ingredient

Salicylic Acid 2%

Purpose

Psoriasis and Seborrheic Dermatitis

Uses

relieves and helps prevent recurrence of skin:

- itching
- irritation
- redness
- flaking
- scaling

due to psoriasis and seborrheic dermatitis

Warnings

For external use only

Ask a doctor before use if condition covers a large area of the body.

When using this product avoid contact with the eyes. If contact occurs, rinse the eyes thoroughly with water.

Stop use and ask a doctor if condition worsens or does not improve after regular use as directed

Keep out of reach of children. If swallowed, get medical help or contact a Poison Control Center immediately.

Directions

Apply to affected areas one to four times daily or as directed by a doctor

Other Information

Store at room temperature 15° - 30°C (59° - 86°F). Keep out of direct sunlight.

Inactive ingredients

WATER, BUTYLENE GLYCOL, CETYL ALCOHOL, ISOPROPYL MYRISTATE, POLYSORBATE 60, STEARIC ACID, DIMETHICONE, GLYCERYL STEARATE, OCTYLDODECANOL, MYRISTOYL/PALMITOYL OXOSTEARAMIDE/ARACHAMIDE
MEA, PANTHENOL, TOCOPHERYL ACETATE, CHOLESTEROL, XANTHAN GUM, METHYLBENZYL METHYLBENZIMIDAZOLE PIPERIDINYLMETHANONE, POLYACRYLAMIDE, C13-14 ISOPARAFFIN, LAURETH-7, SODIUM HYDROXIDE,
METHYLPARABEN, PROPYLPARABEN

Questions?

Visit our website at www.psoriapalm.com

Distributed by:
Neopharm USA, 1 Oyster Bay Drive, Rumson, NJ 07760

Made in Korea